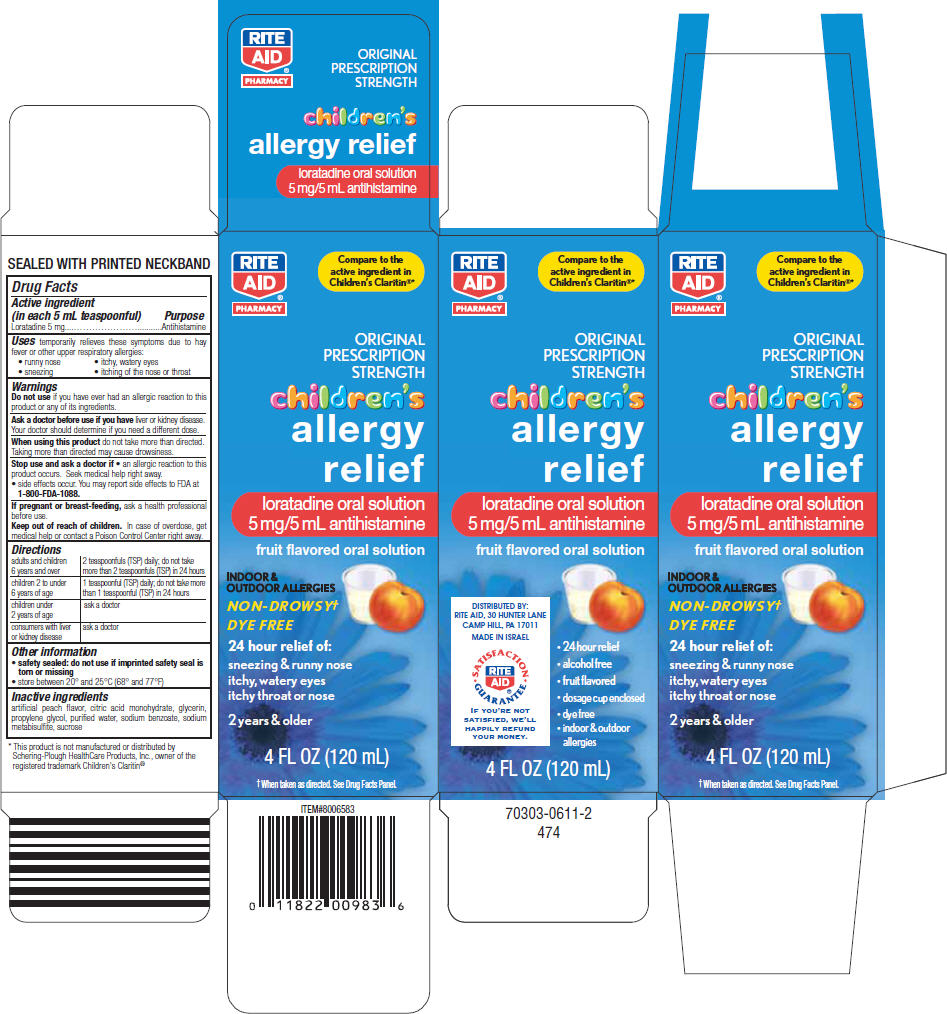 DRUG LABEL: Childrens Allergy Relief
NDC: 11822-0098 | Form: SOLUTION
Manufacturer: Rite Aid Corporation
Category: otc | Type: HUMAN OTC DRUG LABEL
Date: 20121018

ACTIVE INGREDIENTS: Loratadine 5 mg/5 mL
INACTIVE INGREDIENTS: citric acid monohydrate; glycerin; propylene glycol; water; sodium benzoate; sodium metabisulfite; sucrose

Childrens Allergy Relief

Drug Facts

Active ingredient (in each 5 mL teaspoonful)

Loratadine 5 mg

Purpose

Antihistamine

Uses

temporarily relieves these symptoms due to hay fever or other upper respiratory allergies:

- runny nose
- sneezing
- itchy, watery eyes
- itching of the nose or throat

Warnings

Do not use if you have ever had an allergic reaction to this product or any of its ingredients.

Ask a doctor before use if you have liver or kidney disease. Your doctor should determine if you need a different dose.

When using this product do not take more than directed. Taking more than directed may cause drowsiness.

Stop use and ask a doctor if

- an allergic reaction to this product occurs. Seek medical help right away.
- side effects occur. You may report side effects to FDA at 1-800-FDA-1088.

PREGNANCY OR BREAST FEEDING

If pregnant or breast-feeding, ask a health professional before use.

Keep out of reach of children. In case of overdose, get medical help or contact a Poison Control Center right away.

Directions

adults and children 6 years and over | 2 teaspoonfuls (TSP) daily; do not take more than 2 teaspoonfuls (TSP) in 24 hours
children 2 to under 6 years of age | 1 teaspoonful (TSP) daily; do not take more than 1 teaspoonful (TSP) in 24 hours
children under 2 years of age | ask a doctor
consumers with liver or kidney disease | ask a doctor

Other information

- safety sealed: do not use if imprinted safety seal is torn or missing
- store between 20° and 25°C (68° and 77°F)

Inactive ingredients

artificial peach flavor, citric acid monohydrate, glycerin, propylene glycol, purified water, sodium benzoate, sodium metabisulfite, sucrose

DISTRIBUTED BY:
RITE AID, 30 HUNTER LANE
CAMP HILL, PA 17011

PRINCIPAL DISPLAY PANEL - 120 mL Bottle Carton

RITE
AID®
PHARMACY

Compare to the
active ingredient in
Children's Claritin®*

ORIGINAL
PRESCRIPTION
STRENGTH

children's
allergy
relief

loratadine oral solution
5 mg/5 mL antihistamine

fruit flavored oral solution

INDOOR &
OUTDOOR ALLERGIES

NON-DROWSY†

DYE FREE

24 hour relief of:

sneezing & runny nose
itchy, watery eyes
itchy throat or nose

2 years & older

4 FL OZ (120 mL)

† When taken as directed. See Drug Facts Panel.